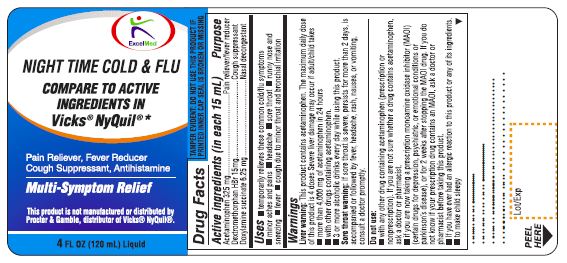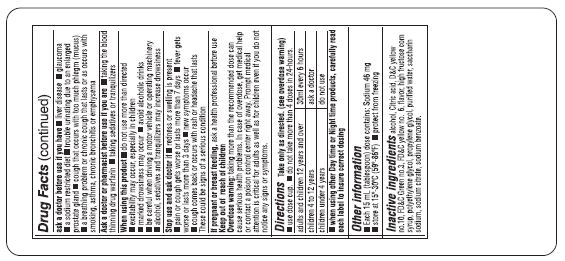 DRUG LABEL: NITETIME COUGH
NDC: 71027-041 | Form: LIQUID
Manufacturer: KINGSTON PHARMA LLC
Category: otc | Type: HUMAN OTC DRUG LABEL
Date: 20190130

ACTIVE INGREDIENTS: ACETAMINOPHEN 325 mg/15 mL; DEXTROMETHORPHAN HYDROBROMIDE 15 mg/15 mL; DOXYLAMINE SUCCINATE 6.25 mg/15 mL
INACTIVE INGREDIENTS: ALCOHOL; ANHYDROUS CITRIC ACID; FD&C BLUE NO. 1; FD&C RED NO. 40; METHYL SALICYLATE; HIGH FRUCTOSE CORN SYRUP; POLYETHYLENE GLYCOL, UNSPECIFIED; PROPYLENE GLYCOL; SACCHARIN SODIUM; SODIUM CITRATE, UNSPECIFIED FORM; WATER

NITETIME COUGH

Active Ingredient (in each 15 mL = 1 tablespoon):
Acetaminophen 325 mg
Dextromethorphan HBr 15 mg
Doxylamine Succinate 6.25 mg

Purpose:
Pain reliever/fever reducer
Cough suppressant
Antihistamine

Uses

- Temporarily relieves these common cold/flu symptoms
  1. Cough due to minor throat and bronchial irritation
  2. Runny nose and sneezing
  3. Minor aches and pains
  4. Headache
  5. Sore throat
  6. Fever

Warnings

Liver warning: This product contains acetaminophen. Severe liver damage may occur if adult/child takes

- More than 4 doses in 24 hours, which is the maximum daily amount for this product.
- With other drugs containing acetaminophen.
- Adult has 3 or more alcoholic drinks every day while using this product.

Sore throat warning: If sore throat is severe, persists for more than 2 days, is accompanied or followed by fever, headache, rash, nausea, or vomiting, consult a doctor promptly.

Do not use:

- With any other drug containing acetaminophen (prescription or nonprescription). If you are not sure whether a drug contains acetaminophen, ask a doctor or pharmacist.
- If you are now taking a prescription monoamine oxidase inhibitor (MAOI) (certain drugs for depression, psychiatric, or emotional conditions or parkinson’s disease), or for 2 weeks after stopping the MAOI drug. If you do not know if your prescription drug contains an MAOI, ask a doctor or pharmacist before taking this product.
- To make a child sleep.

TAMPER EVIDENT: DO NOT USE IF PRINTED SAFETY SEAL ON THE BOTTLE IS BROKEN OR MISSING.

Ask a doctor before use if you have

- Glaucoma
- Liver disease
- Heart disease
- High blood pressure
- Thyroid disease
- Diabetes
- Trouble urinating due to an enlarged prostate gland
- Persistent or chronic cough such as occurs with smoking, asthma or emphysema
- Cough that occurs with too much phlegm (mucus)
- A sodium restricted diet

Ask a doctor or pharmacist before use if you are

- Taking sedatives or tranquilizers
- Taking the blood thinning drug warfarin

When using this product

- Do not exceed recommended dosage
- Excitability may occur especially in children
- Marked drowsiness may occur
- Avoid alcoholic drinks
- Alcohol, sedatives and tranquilizers may increase drowsiness
- Be careful when driving a motor vehicle or operating machinery

Stop use and ask doctor if

- Cough lasts more than 7 days, comes back, or occurs with fever, rash, or headache that lasts.

These could be signs of a serious condition

KEEP OUT OF REACH OF CHILDREN

Keep this and all drugs out of the reach of children. In case of accidental overdose, seek professional assistance or contact a Poison control center right away.

PREGNANCY OR BREAST FEEDING

If pregnant or breast-feeding, ask a health professional before use.

Directions:

- Do not take more than directed.
- Use enclosed dosing cup.
- Do not take more than 4 doses in 24-hours.
- Adults and children 12 years and over: take 2 tablespoons (TBSP) or 30 mL every 6 hours.
- Children 4 to under 12 years: ask a doctor
- Children under 4 years: do not use
- When using other Daytime or Nite time products, carefully read each label to insure correct dosing

Other information

- Store between 15-30 degree Celsius (59-86 degree Fahrenheit)
- Each tablespoon contains: Sodium 46mg

INACTIVE INGREDIENT

Inactive ingredients: Alcohol, Anhydrous citric acid, FD&C blue 1, FD&C red 40, flavor, High fructose corn syrup, Polyethylene glycol, Propylene glycol, Saccharin sodium, Sodium citrate and Purified Water.

HOW SUPPLIED

(packs: 4oz, 6oz, 10oz & 12oz) Kingston NDC# 71027-041-06
Manufactured by: Kingston Pharma LLC
5 County Route 42
Massena, NY 13662